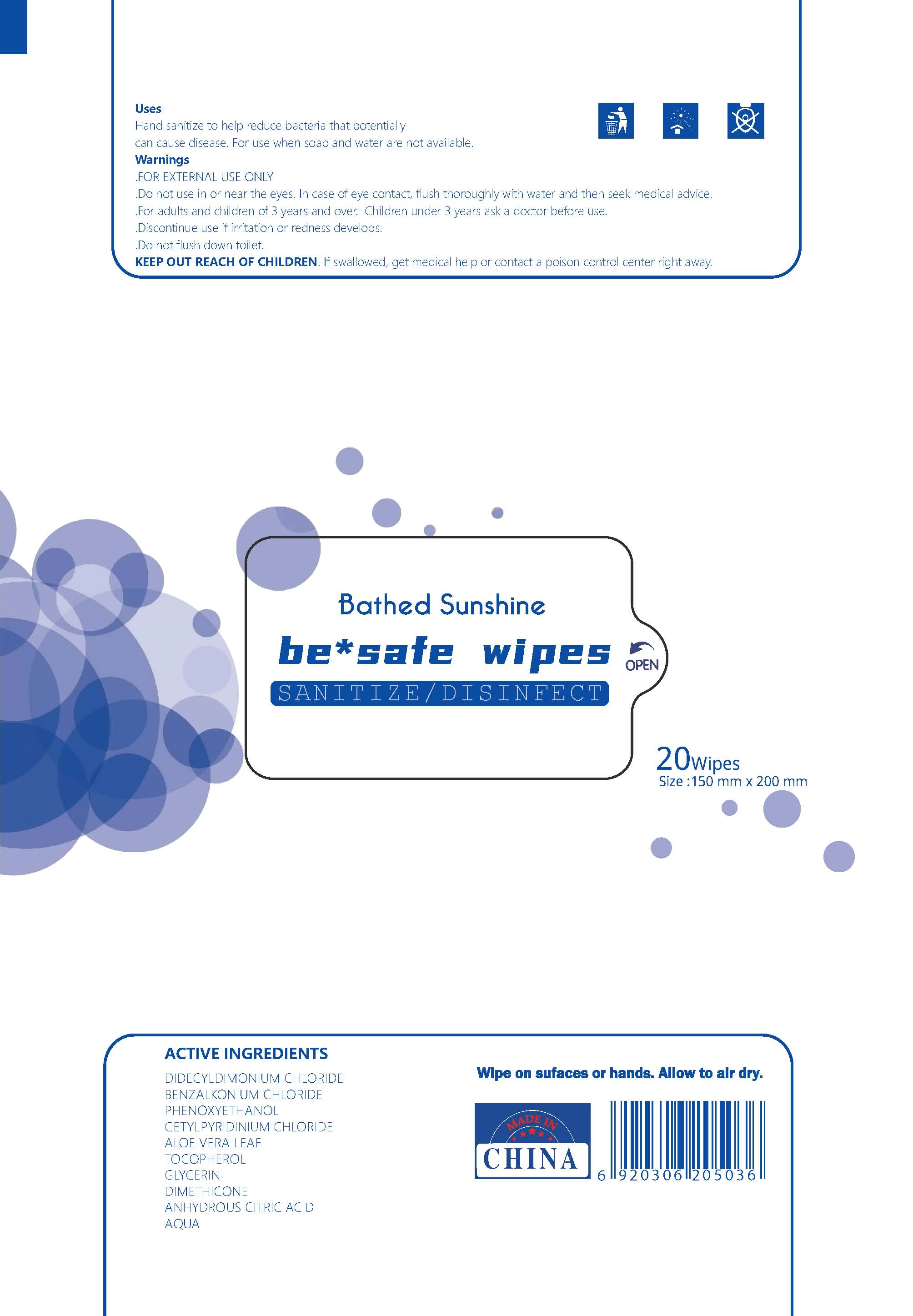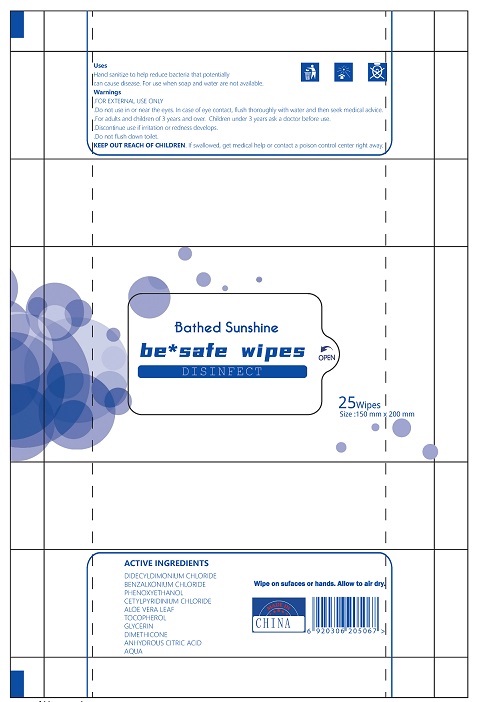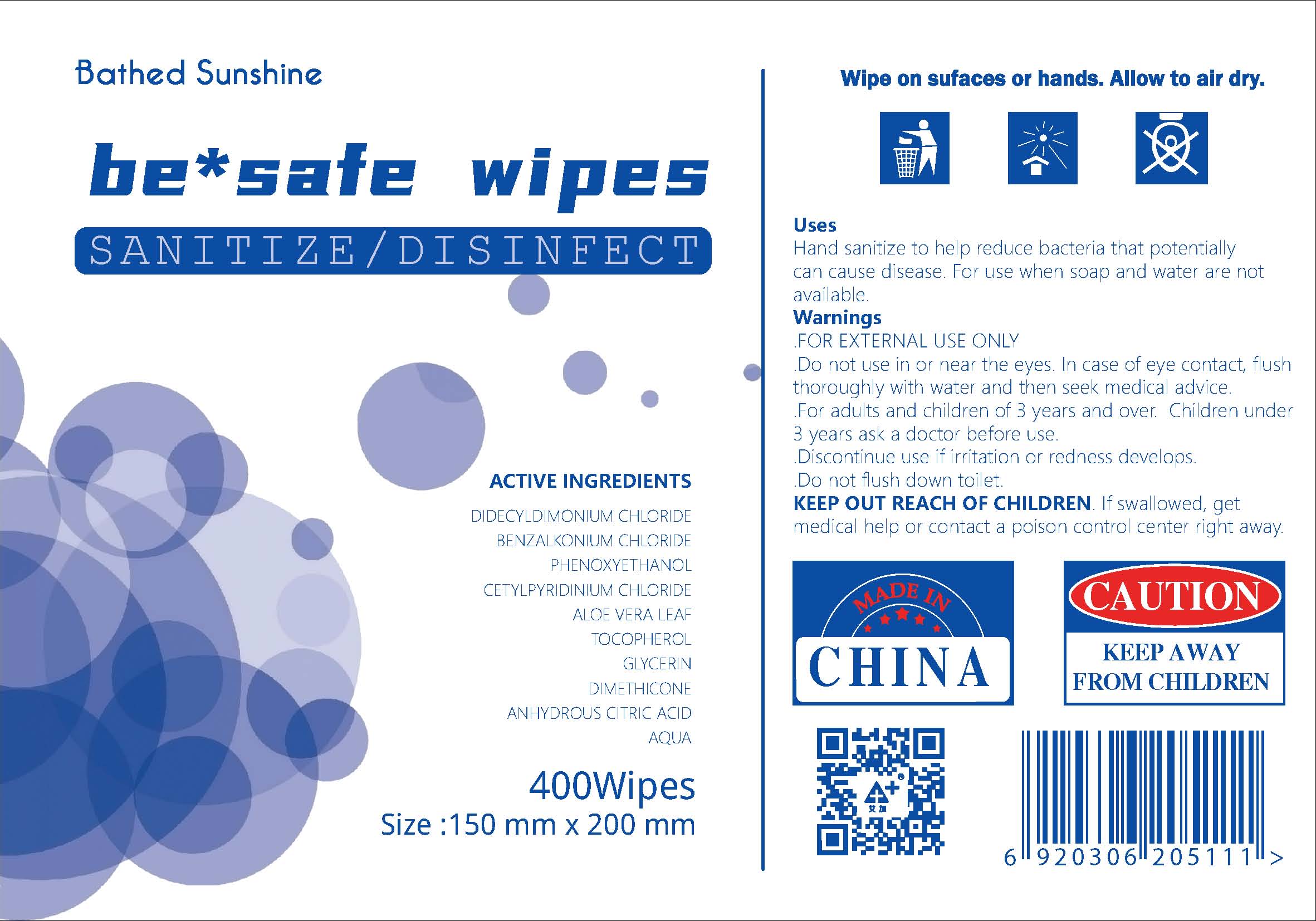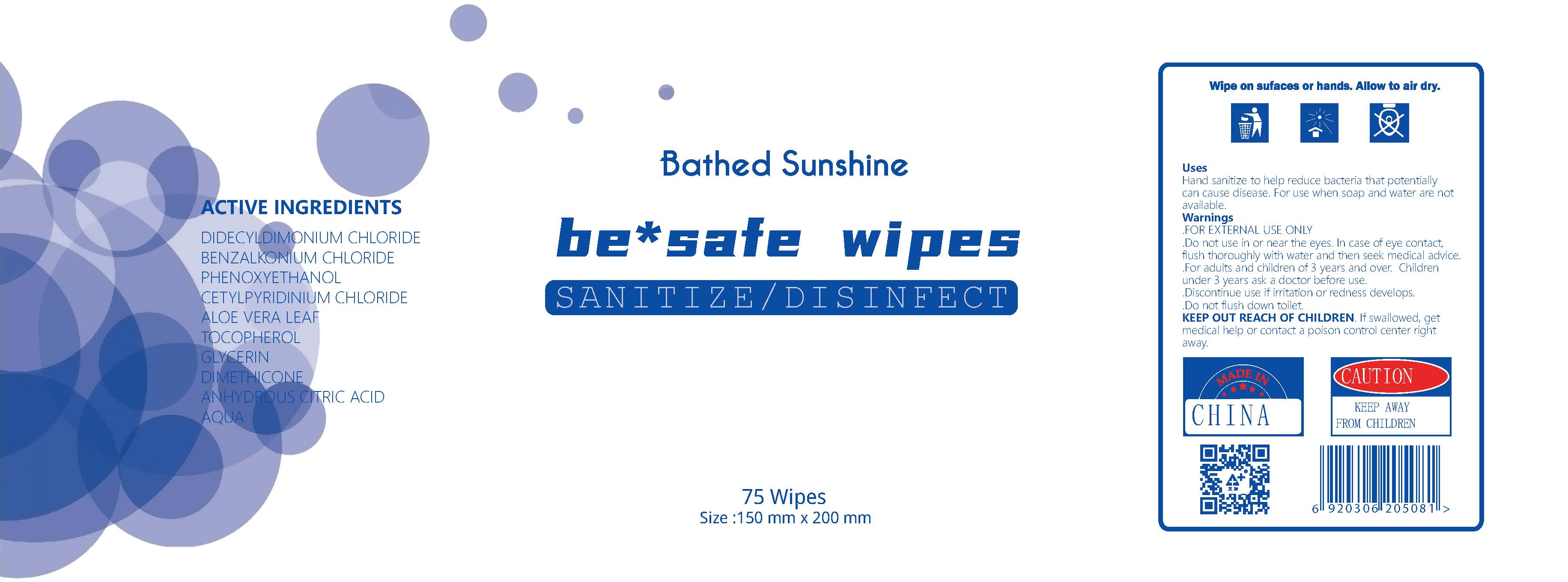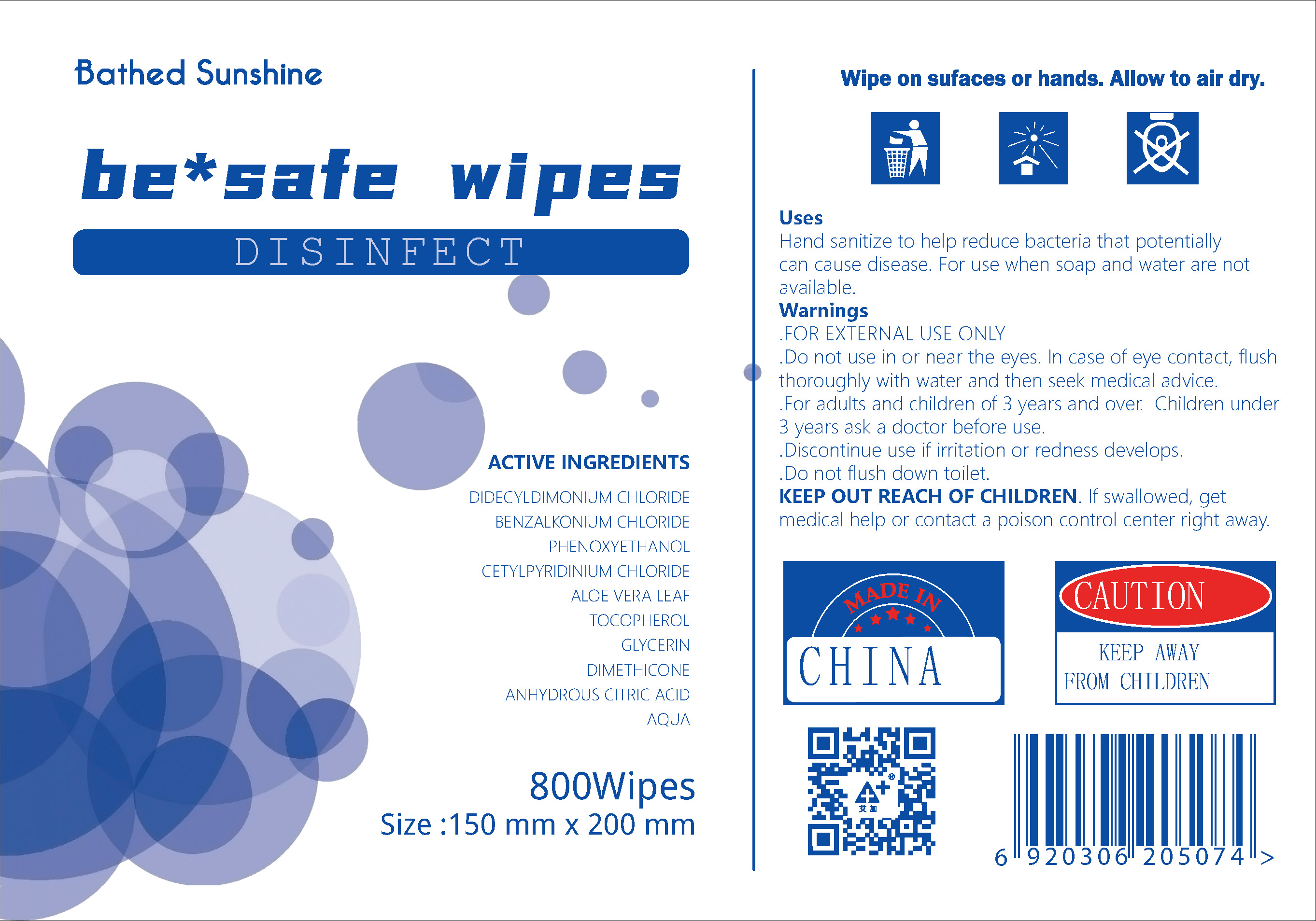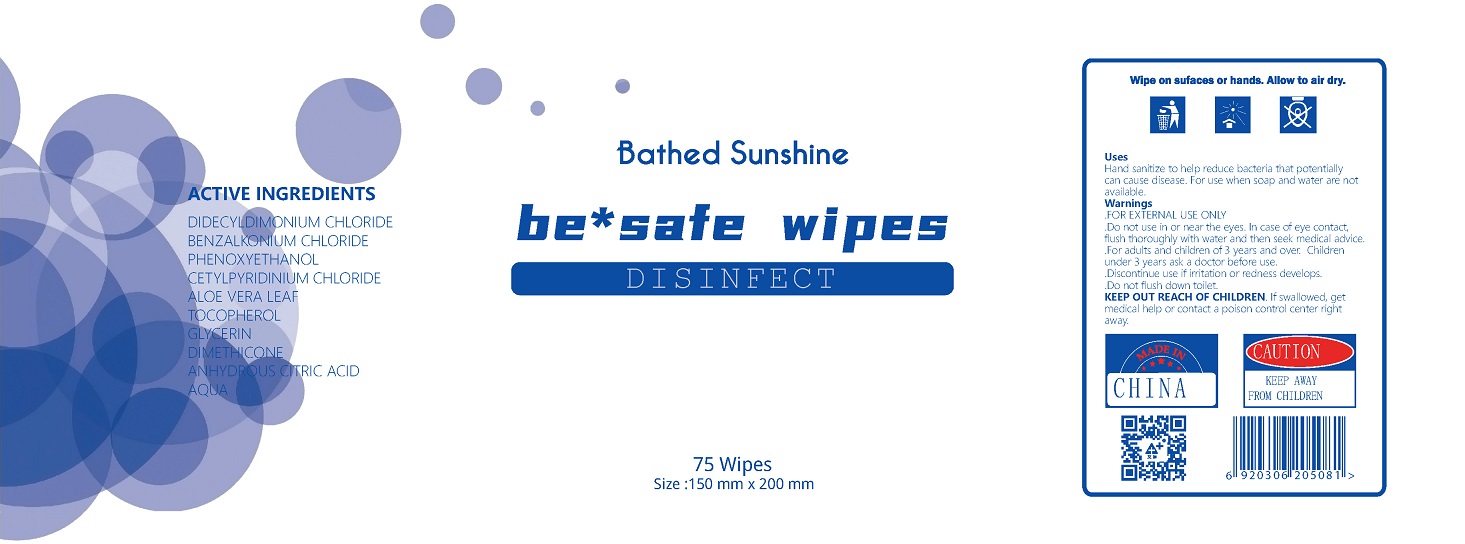 DRUG LABEL: Sanitize/Disinfect Wipes
NDC: 69733-100 | Form: CLOTH
Manufacturer: JIANGSU TERRA MEDICAL TECHNOLOGY CO LTD
Category: otc | Type: HUMAN OTC DRUG LABEL
Date: 20200628

ACTIVE INGREDIENTS: GLYCERIN 0.01 1/100 1; PHENOXYETHANOL 0.2 1/100 1; CETYLPYRIDINIUM CHLORIDE 0.03 1/100 1; BENZALKONIUM CHLORIDE 0.4 1/100 1; DIDECYLDIMONIUM CHLORIDE 0.2 1/100 1; ANHYDROUS CITRIC ACID 0.01 1/100 1; TOCOPHEROL 0.0025 1/100 1; ALOE VERA LEAF 0.0025 1/100 1; DIMETHICONE 0.5 1/100 1
INACTIVE INGREDIENTS: WATER

This is a disinfect wipes.

The firm does not add other active or inactive ingredients. Different or additional ingredients may impact the quality and potency of the product.

Active Ingredient(s)

DIDECYLDIMONIUM CHLORIDE Purpose: Antiseptic
BENZALKONIUM CHLORIDE Purpose: Antiseptic
PHENOXYETHANOL Purpose: Antiseptic
CETYLPYRIDINIUM CHLORIDE Purpose: Antiseptic
ALOE VERA LEAF Purpose: Antiseptic
TOCOPHEROL Purpose: Antiseptic
GLYCERIN Purpose: Antiseptic
DIMETHICONE Purpose: Antiseptic
ANHYDROUS CITRIC ACID Purpose: Antiseptic

Purpose

Antiseptic, disinfect wipes

Use

Disinfect wipes used to help reduce bacteria that potentially can cause disease.For use when soap and water are not available.

Warnings

For external use only. Do not use in or near he eyes, in case of eye contact, flush thoroughly with water and then seek medical advice.

For adults and children of 3 years and over. Children under 3 years ask a doctore before use.

Discontinue use if irritation or redness develops. Do not flush down toilet.

Keep out reach of children. If swallowed, get medical help or contact poison control center right away.

Do not use

- Children under 3 years ask a doctore before use.
- on open skin wounds
- Do not use in or near he eyes, in case of eye contact, flush thoroughly with water and then seek medical advice.

When using this product keep out of eyes, ears, and mouth. In case of contact with eyes, rinse eyes thoroughly with water.
Stop use and ask a doctor if irritation or rash occurs. These may be signs of a serious condition.
Keep out of reach of children. If swallowed, get medical help or contact a Poison Control Center right away.

Stop use and ask a doctor if irritation or or redness develops occurs. These may be signs of a serious condition.

Keep out of reach of children. If swallowed, get medical help or contact a Poison Control Center right away.

Directions

- Wipe on surfaces or hands.Allow to air dry.
- Supervise children under 3 years of age when using this product to avoid swallowing.

Other information

- Store between 15-30C (59-86F)
- Avoid freezing and excessive heat above 40C (104F)

Inactive ingredients

non

Package Label - Principal Display Panel

20pcs 69733-400-01

400 pcs 69733-600-01

75 pcs 69733-500-01

69733-100-01

69733-200-01 69733-300-01

69733-300-02 69733-100-02